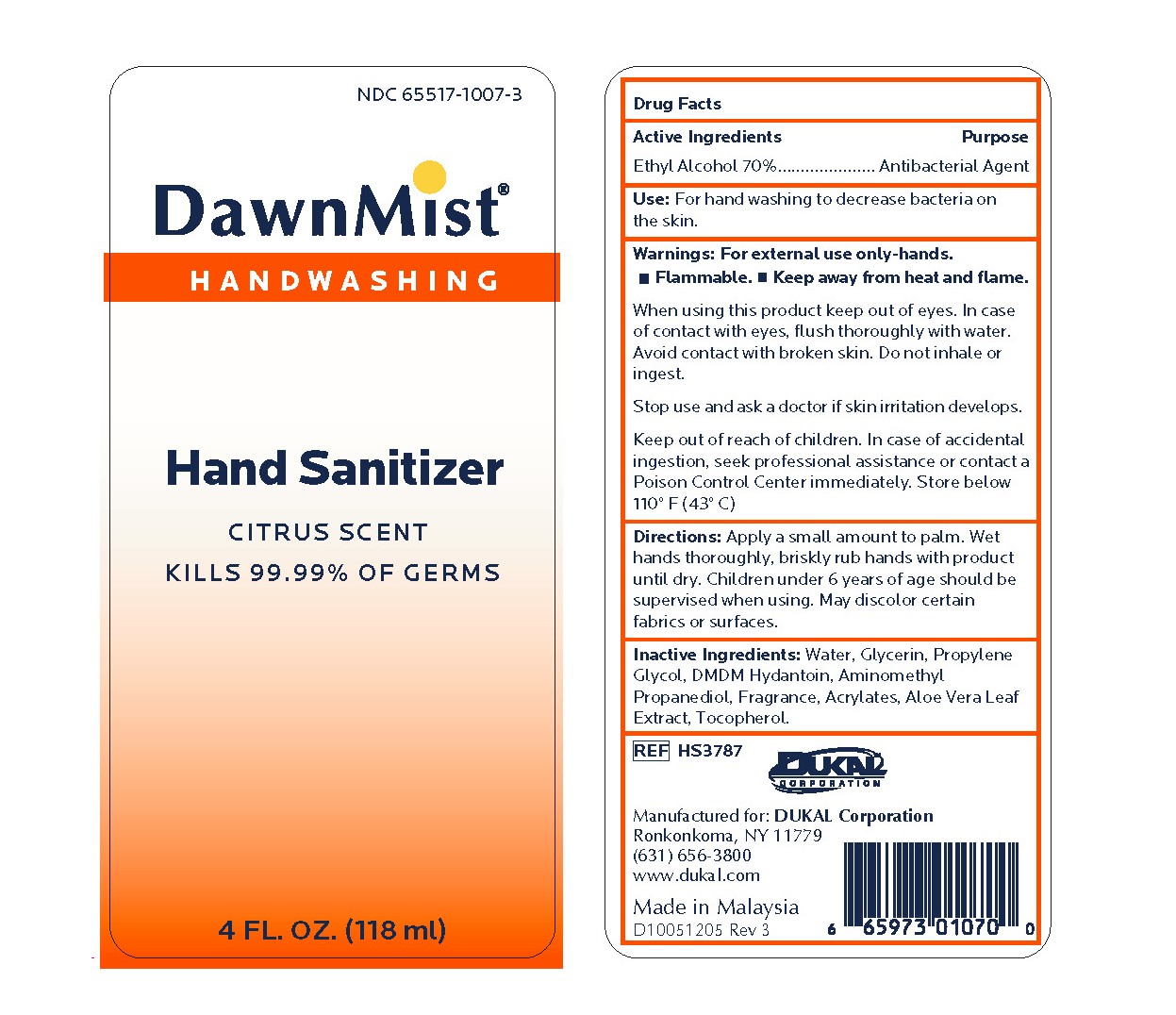 DRUG LABEL: DawnMist Alcohol Hand Sanitizer
NDC: 65517-1007 | Form: GEL
Manufacturer: Dukal LLC
Category: otc | Type: HUMAN OTC DRUG LABEL
Date: 20231013

ACTIVE INGREDIENTS: ALCOHOL 700 mg/1 mL
INACTIVE INGREDIENTS: WATER; GLYCERIN; PROPYLENE GLYCOL; DMDM HYDANTOIN; AMINOMETHYL PROPANEDIOL; ALOE VERA LEAF; TOCOPHEROL

DawnMist Alcohol Hand Sanitizer

Active Ingredient

Ethyl Alcohol 70%

Purpose

Antibacterial Agent

Use:

For hand washing to decrease bacteria on skin.

Warnings

Flammable.
Keep away from heat or flame.
For external use only.

Do not use in the eyes ■ In rare instances of irritation,
discontinue use if irritation and redness develop ■ If
condition persists for more than 72 hours, consult a
physician

Keep out of reach of children.

■ If swallowed, contact a physician or poison center ■ Use only as directed

Directions:

To decrease bacteria on skin, apply a small amount to palm. Briskly rub covering hands with product until dry.

Inactive Ingredients:

Water, Glycerin, Propylene Glycol, DMDM Hydantoin, Aminomethyl Propanediol, Fragrance, Acrylates/C10-30 Alkyl Acrylate Crosspolymer, Aloe Vera Leaf Extract, Tocopherol

Package Label

NDC 65517-1007-3

DawnMist

Handwashing

Hand Sanitizer

Citrus Scent
Kills 99.99% of Germs
4 FL. OZ. (118ml)